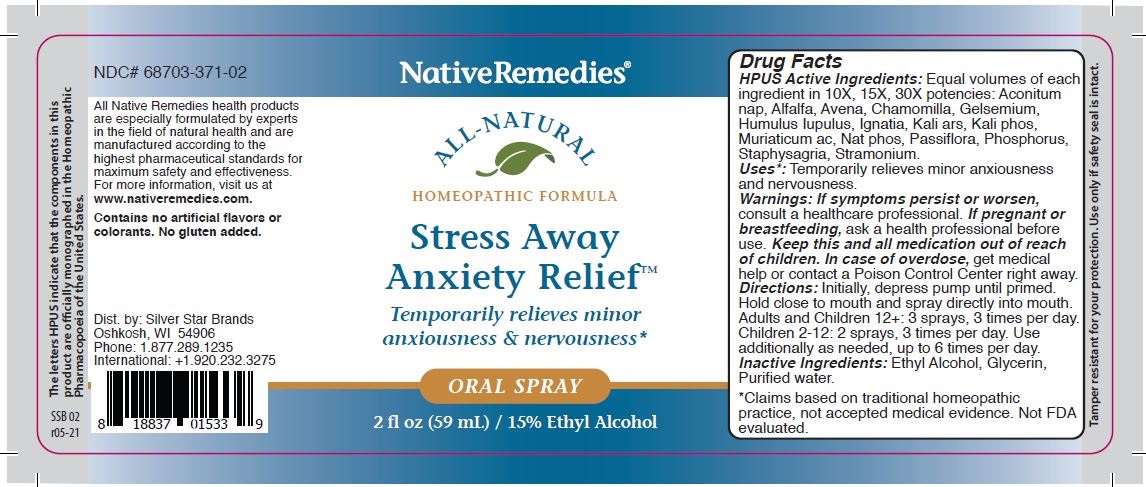 DRUG LABEL: Stress Away Anxiety Relief
NDC: 68703-371 | Form: SPRAY
Manufacturer: Silver Star Brands
Category: homeopathic | Type: HUMAN OTC DRUG LABEL
Date: 20250101

ACTIVE INGREDIENTS: AVENA SATIVA LEAF 30 [hp_X]/59 mL; MATRICARIA CHAMOMILLA FLOWERING TOP OIL 30 [hp_X]/59 mL; SODIUM PHOSPHATE, DIBASIC 30 [hp_X]/59 mL; ALFALFA 30 [hp_X]/59 mL; POTASSIUM ARSENITE ANHYDROUS 30 [hp_X]/59 mL; DATURA STRAMONIUM 30 [hp_X]/59 mL; PASSIFLORA INCARNATA FLOWERING TOP 30 [hp_X]/59 mL; ACONITUM NAPELLUS 30 [hp_X]/59 mL; HYDROCHLORIC ACID 30 [hp_X]/59 mL; PHOSPHORUS 30 [hp_X]/59 mL; STRYCHNOS IGNATII WHOLE 30 [hp_X]/59 mL; GELSEMIUM SEMPERVIRENS ROOT 30 [hp_X]/59 mL; DELPHINIUM STAPHISAGRIA SEED 30 [hp_X]/59 mL; POTASSIUM PHOSPHATE, DIBASIC 30 [hp_X]/59 mL; HUMULUS LUPULUS WHOLE 30 [hp_X]/59 mL
INACTIVE INGREDIENTS: ALCOHOL; WATER; GLYCERIN

Stress Away Anxiety Relief

ACTIVE INGREDIENT

HPUS Active Ingredients: Equal volumes of each ingredient in 10X, 15X, 30X potencies: Aconitum nap, Alfalfa, Avena, Chamomilla, Gelsemium, Humulus Iupulus, Ignatia, Kali ars, Kali phos, Muriaticum ac, Nat phos, Passiflora, Phosphorus, Staphysagria, Stramonium.

The letters HPUS indicate that the components in this product are officially monographed in the Homeopathic Pharmacopoeia of the United States.

Uses*

Uses*: Temporarily relieves minor anxiousness and nervousness.

*Claims based on traditional homeopathic practice, not accepted medical evidence. Not FDA evaluated.

Warnings

Warnings: If symptoms persist or worsen, consult a healthcare professional. If pregnant or breastfeeding, ask a health professional before use. Keep this and all medication out of reach of children. In case of overdose, get medical help or contact Poison Control Center right away.

Directions

Directions: Initially, depress pump until primed. Hold close to mouth and spray directly into mouth. Adults and children 12+: 3 sprays, 3 times per day. Children 2-12: 2 sprays, 3 times per day. Use additionally as needed, up to 6 times per day.

OTHER SAFETY INFORMATION

Contains no artificial flavors or colorants. No gluten added.

Tamper resistant for your protection. Use only if safety seal is intact.

Inactive ingredients

Inactive Ingredients: Ethyl Alcohol, Glycerin, Purified Water.

KEEP OUT OF REACH OF CHILDREN

Keep this and all medication out of reach of children.

PREGNANCY OR BREAST FEEDING

If pregnant or breastfeeding, ask a health professional before use.

PURPOSE

Temporarily relieves minor anxiousness & nervousness.